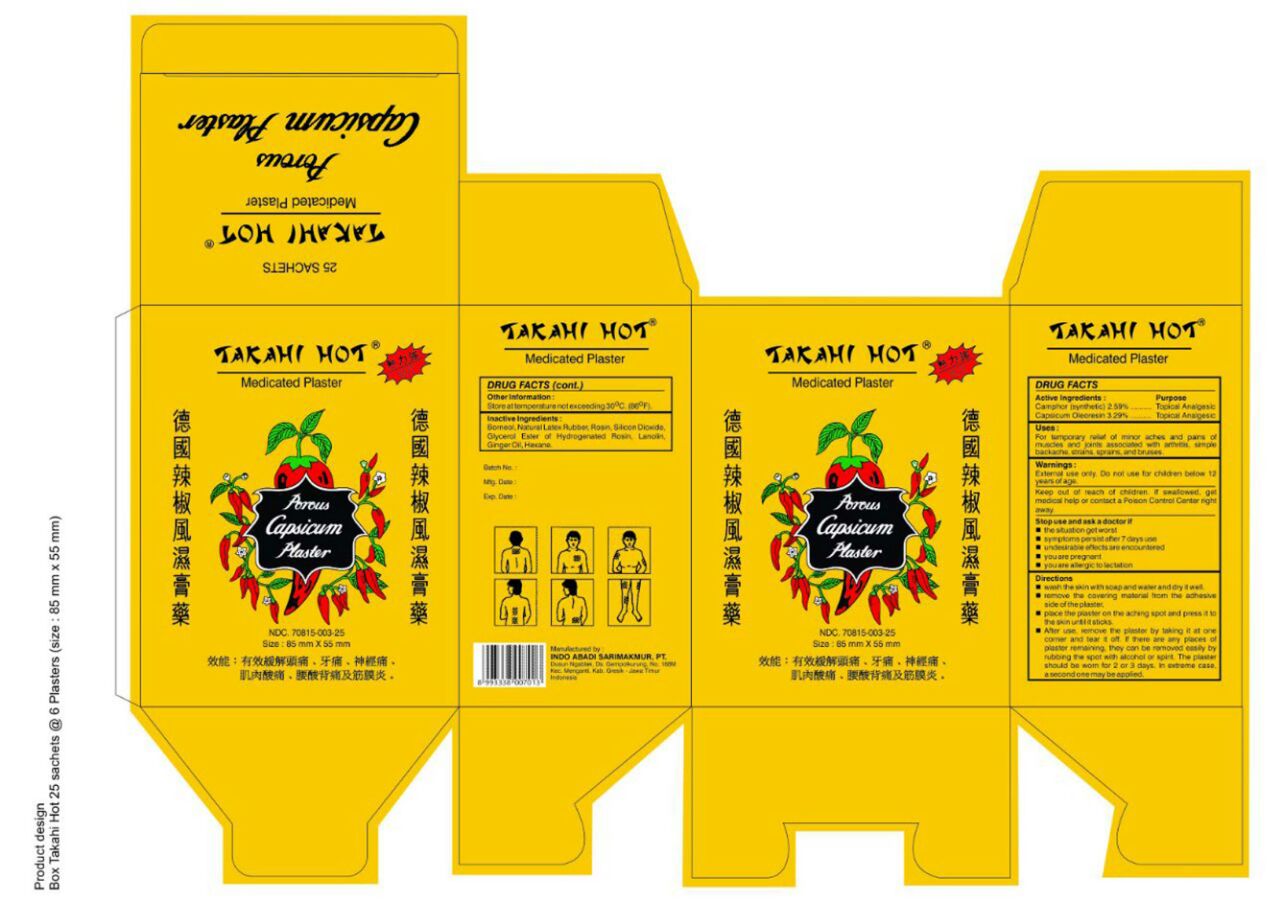 DRUG LABEL: Takahi Hot Medicated Plaster
NDC: 70815-003 | Form: PLASTER
Manufacturer: Indo Abadi Sari Makmur, PT
Category: otc | Type: HUMAN OTC DRUG LABEL
Date: 20220114

ACTIVE INGREDIENTS: CAMPHOR (SYNTHETIC) 2.59 g/100 g; CAPSICUM OLEORESIN 3.29 g/100 g
INACTIVE INGREDIENTS: BORNEOL; NATURAL LATEX RUBBER; ROSIN; SILICON DIOXIDE; GLYCEROL ESTER OF HYDROGENATED ROSIN; LANOLIN; GINGER OIL; HEXANE

Indo Abadi Sari Makmur, PT

Active Ingredients

Camphor (Synthetic) 2.59%

Capsicum Oleoresin 3.29%

Purpose

Camphor (Synthetic) Topical Analgesic
Capsicum Oleoresin Topical Analgesic

Uses

For temporary relief of minor aches and pains of muscles and joints associated with arthritis, simple backache, strains, sprains, and bruises.

DIRECTIONS

- Wash the skin with soap and water; and dry it well.
- Remove the covering material from the adhesive side of the plaster.
- Place the plaster on the aching spot and press it to the skin until it sticks.
- After use, remove the plaster by taking it at one corner and tear it off. If there are any places of plaster remaining, they can be removed easily by rubbing the spot with alcohol or spirit. The plaster should be worn for 2 or 3 days. In extreme case, a second one may be applied.

Warnings

External Use Only. Do not use for children below 12 years of age.

Warnings

Keep out of reach of children. If swallowed, get medical help or contact a Poison Control Center right away.

Stop Use and Ask a Doctor If

- the situation gets worst.
- symptoms persist after 7 days use.
- if undesirable effects are encountered.
- if you are pregnant.
- you are allergic to lactation.

Other Information

Store at temperature not exceeding 30°C (86°F).

Manufactured by

INDO ABADI SARIMAKMUR, PT.
Dusun Ngablak, Ds. Gempolkurung, No. 168M
Kec. Menganti, Kab. Gresik - Jawa Timur
Indonesia

Inactive Ingredients

BORNEOL, NATURAL LATEX RUBBER, ROSIN, SILICON DIOXIDE, GLYCEROL ESTER OF HYDROGENATED ROSIN, LANOLIN, GINGER OIL, HEXANE